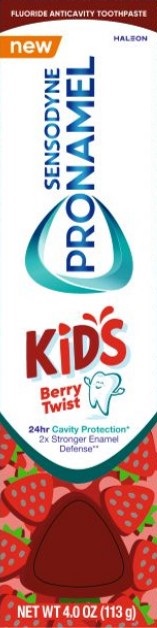 DRUG LABEL: Sensodyne Pronamel
NDC: 0135-0809 | Form: PASTE
Manufacturer: Haleon US Holdings LLC
Category: otc | Type: HUMAN OTC DRUG LABEL
Date: 20250703

ACTIVE INGREDIENTS: SODIUM FLUORIDE 1.10 mg/1 g
INACTIVE INGREDIENTS: WATER; SORBITOL; HYDRATED SILICA; GLYCERIN; POLYETHYLENE GLYCOL 400; COCAMIDOPROPYL BETAINE; XANTHAN GUM; SACCHARIN SODIUM; SODIUM HYDROXIDE; D&C RED NO. 30

Drug Facts

Active ingredient

Sodium fluoride 0.254% (0.15% w/v fluoride ion)

Purpose

Anticavity

Use

- aids in the prevention of dental cavities.

Warnings

Keep out of the reach of children under 6 years of age.

If more than used for brushing is accidentally swallowed, get medical help or contact a Poison Control Center right away.

Directions

- adults and children 2 years of age and older:
  - brush teeth thoroughly, preferably after each meal or at least twice a day, and not more than 3 times a day, or as directed by a dentist or doctor. Minimize swallowing. Spit out after brushing.
  - to minimize swallowing for children under 6 years of age, use a pea-sized amount and rinsing until good habits are established.
- children under 2 years of age: Consult a dentist or doctor.

Other information

- do not store above 25°C (77°F)

Inactive ingredients

water, sorbitol, hydrated silica, glycerin, PEG-8, cocamidopropyl betaine, xanthan gum, flavor, sodium saccharin, sodium hydroxide, red 30

Questions or comments?

1-866-844-2797

ALWAYS FOLLOW THE LABEL

Principal Display Panel

FLUORIDE ANTICAVITY TOOTHPASTE

new HALEON

Sensodyne PRONAMEL

KIDS

Berry Twist

24hr Cavity Protection*

2x Stronger Enamel Defense**

NET WT 4.0 OZ (113 g)

62000000212335 Front Label